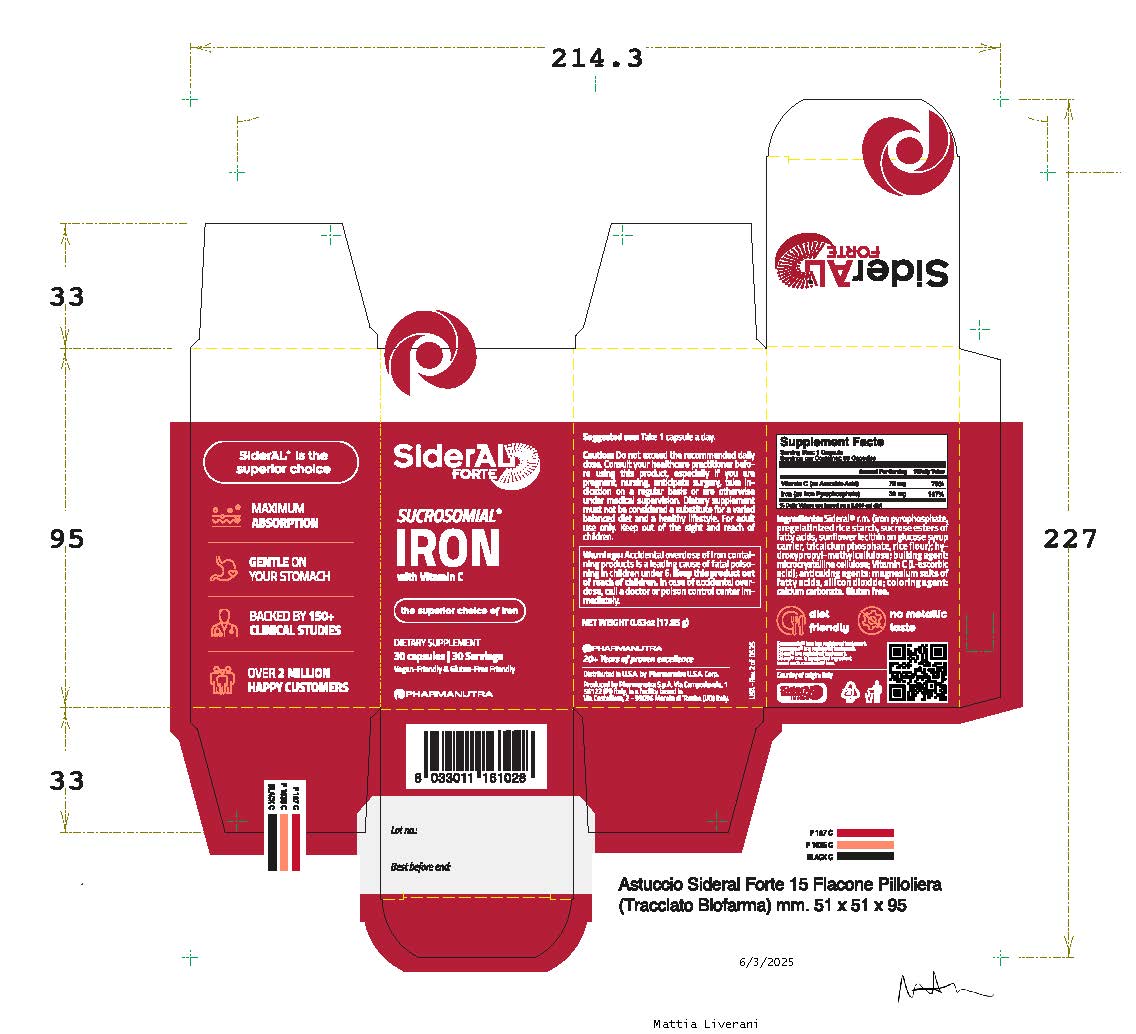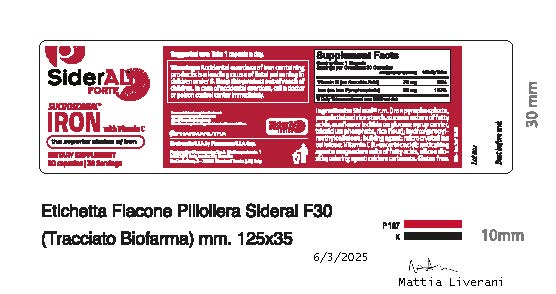 DRUG LABEL: SiderAL
NDC: 84797-001 | Form: CAPSULE, GELATIN COATED
Manufacturer: PharmaNutra Usa Corp.
Category: other | Type: Dietary Supplement
Date: 20250609

ACTIVE INGREDIENTS: IRON 30 mg/1 mg; ASCORBIC ACID 70 mg/1 mg
INACTIVE INGREDIENTS: SILICON DIOXIDE; CALCIUM CARBONATE; HYDROXYPROPYL METHYLCELLULOSE; MICROCRYSTALLINE CELLULOSE; TAPIOCA STARCH; MAGNESIUM PALMITOSTEARATE

SiderAL Forte
Sucrosomial
Iron
with Vitamin C

STATEMENT OF IDENTITY

Supplement Facts
Serving Size: 1 capsule a day
Serving per container: 30
Amount per Serving % Daily Value

Vitamin C (as Ascorbic Acid) 70 mg 78%

Iron (as Iron Pyrophosphate) 30 mg 167%

DOSAGE AND ADMINISTRATION

Suggested use: Take 1 capsule a day.

HEALTH CLAIM

Maximum Absorption

Backed by 150+ clinical studies

WARNINGS

Warnings: Accidental overdose of iron containing products is a leading cause of fatal poisoning in children under 6. Keep this product out of reach of children. In case of accidental overdose, call a doctor or poison control center immediately.

PRECAUTIONS

Caution: Do not exceed the recommended daily dose. Consult your healthcare practitioner before using this product, especially if you are pregnant, nursing, anticipate surgery, take indication on a regular basis or are otherwise under medical supervision. Dietary supplement must not be considered a substitute for a varied balanced diet and a healthy lifestyle. For adult use only. Keep out of the sight and reach of children.